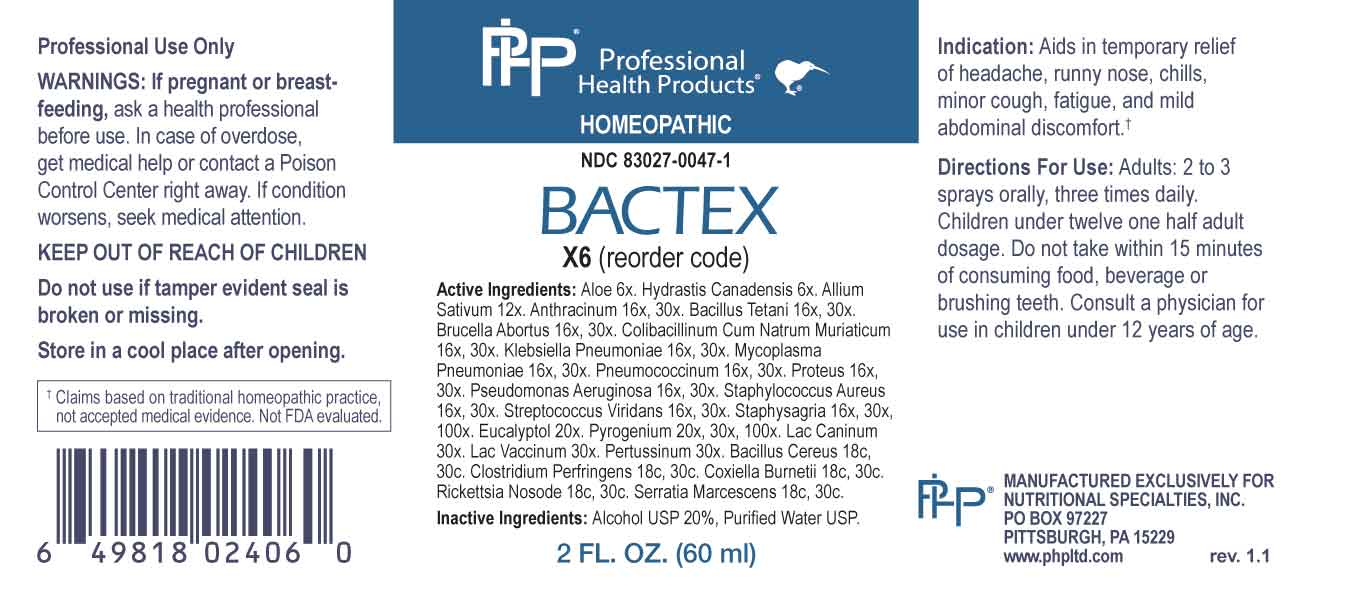 DRUG LABEL: Bactex
NDC: 83027-0047 | Form: SPRAY
Manufacturer: Nutritional Specialties, Inc.
Category: homeopathic | Type: HUMAN OTC DRUG LABEL
Date: 20230915

ACTIVE INGREDIENTS: ALOE 6 [hp_X]/1 mL; GOLDENSEAL 6 [hp_X]/1 mL; GARLIC 12 [hp_X]/1 mL; BACILLUS ANTHRACIS IMMUNOSERUM RABBIT 16 [hp_X]/1 mL; CLOSTRIDIUM TETANI 16 [hp_X]/1 mL; BRUCELLA ABORTUS 16 [hp_X]/1 mL; ESCHERICHIA COLI 16 [hp_X]/1 mL; KLEBSIELLA PNEUMONIAE 16 [hp_Q]/1 mL; MYCOPLASMA PNEUMONIAE 16 [hp_X]/1 mL; STREPTOCOCCUS PNEUMONIAE 16 [hp_X]/1 mL; PROTEUS VULGARIS 16 [hp_X]/1 mL; PSEUDOMONAS AERUGINOSA 16 [hp_X]/1 mL; STAPHYLOCOCCUS AUREUS 16 [hp_X]/1 mL; STREPTOCOCCUS VIRIDANS GROUP 16 [hp_X]/1 mL; DELPHINIUM STAPHISAGRIA SEED 16 [hp_X]/1 mL; EUCALYPTOL 20 [hp_X]/1 mL; RANCID BEEF 20 [hp_X]/1 mL; CANIS LUPUS FAMILIARIS MILK 30 [hp_X]/1 mL; COW MILK 30 [hp_X]/1 mL; HUMAN SPUTUM, BORDETELLA PERTUSSIS INFECTED 30 [hp_X]/1 mL; BACILLUS CEREUS 18 [hp_C]/1 mL; CLOSTRIDIUM PERFRINGENS 18 [hp_C]/1 mL; COXIELLA BURNETII 18 [hp_C]/1 mL; RICKETTSIA PROWAZEKII 18 [hp_C]/1 mL; SERRATIA MARCESCENS 18 [hp_C]/1 mL
INACTIVE INGREDIENTS: WATER; ALCOHOL

DRUG FACTS:

ACTIVE INGREDIENTS:

Aloe 6X, Hydrastis Canadensis 6X, Allium Sativum 12X, Anthracinum 16X, 30X, Bacillus Tetani 16X, 30X, Brucella Abortus 16X, 30X, Colibacillinum Cum Natrum Muriaticum 16X, 30X, Klebsiella Pneumoniae 16X, 30X, Mycoplasma Pneumoniae 16X, 30X, Pneumococcinum 16X, 30X, Proteus 16X, 30X, Pseudomonas Aeruginosa 16X, 30X, Staphylococcus Aureus 16X, 30X, Streptococcus Viridans 16X, 30X, Staphysagria 16X, 30X, 100X, Eucalyptol 20X, Pyrogenium 20X, 30X, 100X, Lac Caninum 30X, Lac Vaccinum 30X, Pertussinum 30X, Bacillus Cereus 18C, 30C, Clostridium Perfringens 18C, 30C, Coxiella Burnetii 18C, 30C, Rickettsia Nosode 18C, 30C, Serratia Marcescens 18C, 30C.

PURPOSE:

Aids in temporary relief of headaches, runny nose, chills, minor cough, fatigue, and mild abdominal discomfort.†

†Claims based on traditional homeopathic practice, not accepted medical evidence. Not FDA evaluated.

WARNINGS:

Professional Use Only

If pregnant or breast-feeding, ask a health professional before use.

In case of overdose, get medical help or contact a Poison Control Center right away.

If condition worsens, seek medical attention.

KEEP OUT OF REACH OF CHILDREN

Do not use if tamper evident seal is broken or missing.

Store in a cool place after opening

KEEP OUT OF REACH OF CHILDREN:

In case of overdose, get medical help or contact a Poison Control Center right away.

DIRECTIONS:

Adults: 2 to 3 sprays orally, three times daily. Children under twelve one half adult dosage. Do not take within 15 minutes of consuming food, beverage or brushing teeth. Consult a physician for use in children under 12 years of age.

INDICATIONS:

Aids in temporary relief of headaches, runny nose, chills, minor cough, fatigue, and mild abdominal discomfort.†

†Claims based on traditional homeopathic practice, not accepted medical evidence. Not FDA evaluated.

INACTIVE INGREDIENTS:

Alcohol USP 20%, Purified Water USP.

QUESTIONS:

MANUFACTURED EXCLUSIVELY FOR

NUTRITIONAL SPECIALTIES, INC.

PO BOX 97227

PITTSBURG, PA 15229

www.phpltd.com

PACKAGE LABEL DISPLAY:

Professional

Health Products

HOMEOPATHIC

NDC 83027-0047-1

BACTEX

2 FL. OZ (60 ml)